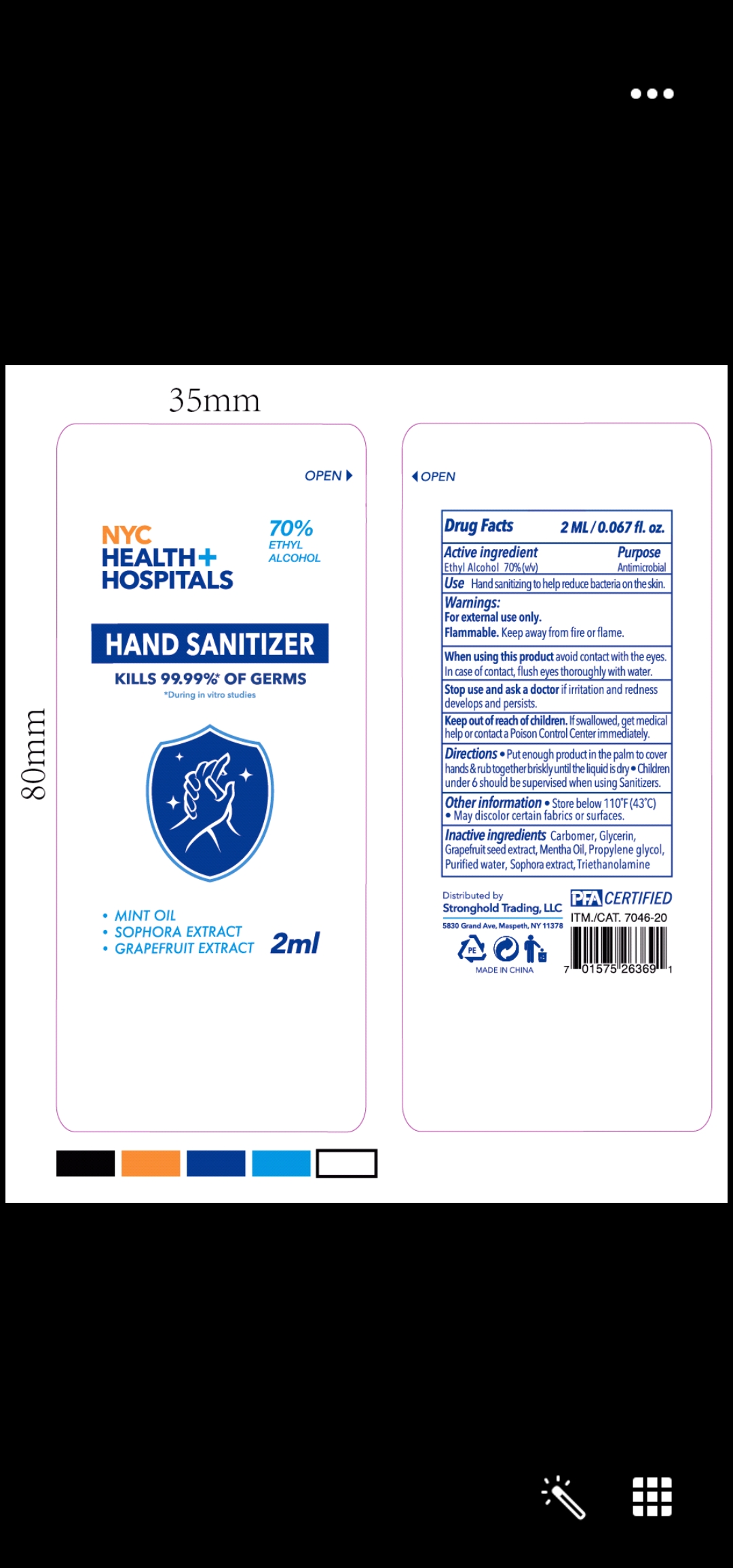 DRUG LABEL: PFA
NDC: 72119-005 | Form: GEL
Manufacturer: BLUE SEA AEROSOL & DAILY CARE CO., LTD
Category: otc | Type: HUMAN OTC DRUG LABEL
Date: 20210602

ACTIVE INGREDIENTS: ALCOHOL 80 mL/100 mL
INACTIVE INGREDIENTS: CARBOMER HOMOPOLYMER, UNSPECIFIED TYPE; PEPPERMINT OIL; SOPHORA FLAVESCENS ROOT; TROLAMINE; PROPYLENE GLYCOL; CITRUS PARADISI SEED; GLYCERIN; WATER

NYC Health+ Hospitals Hand Sanitizer

This is a hand sanitizer manufactured according to the Temporary Policy for Preparation of Certain Alcohol-Based Hand Sanitizer Products During the Public Health Emergency (CoViD-19); Guidance for Industry.

The hand sanitizer is manufactured using only the following United States Pharmacopoeia (USP) grade ingredients in the preparation of the product (percentage in final product formulation) consistent with World Health Organization (WHO) recommendations:

1. Alcohol (ethanol) (USP or Food Chemical Codex (FCC) grade) (80%, volume/volume (v/v)) in an aqueous solution denatured according to Alcohol and Tobacco Tax and Trade Bureau regulations in 27 CFR part 20.
2. Glycerol (1.45% v/v).
3. Hydrogen peroxide (0.125% v/v).
4. Sterile distilled water or boiled cold water.

The firm does not add other active or inactive ingredients. Different or additional ingredients may impact the quality and potency of the product.

Active Ingredient(s)

Ethyl Alcohol 70%(v/v)

Purpose

Purpose: Antimicrobial

Use

Hand sanitizing to help reduce bacteria on the skin.

Warnings

For external use only. Flammable. Keep away from fire or flame

When using this product avoid contact with the eyes. In case of contact, flush eyes thoroughly with water.

Stop use and ask a doctor if irritation and redness develops or persists.

Keep out of reach of children. If swallowed, get medical help or contact a Poison Control Center immediately.

Directions

- Put enough product in the palm to cover hands & rub together briskly until the liquid is dry
- Children under 6 should be supervised when using Sanitizers.

Other information

- Store below 110F (43C)
- May discolor certain fabrics or surfaces.

Inactive ingredients

Carbomer, Glycerin, Grapefruit seed extract, Mentha Oil, Propylene glycol, Purified water, Sophora extract, Triethanolamine